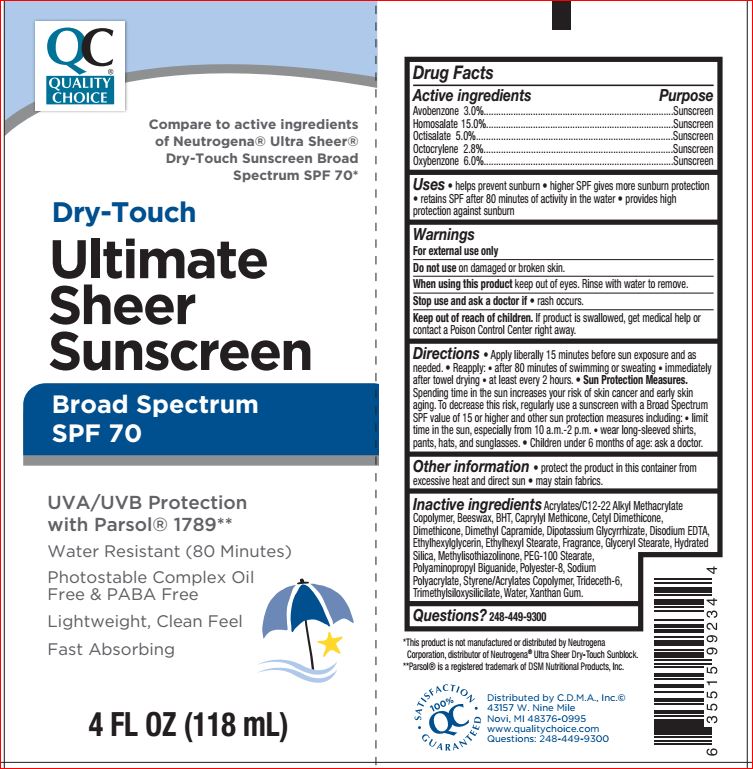 DRUG LABEL: Ultimate Sheer Sunscreen SPF 70
NDC: 63868-781 | Form: LOTION
Manufacturer: Quality Choice
Category: otc | Type: HUMAN OTC DRUG LABEL
Date: 20180607

ACTIVE INGREDIENTS: Avobenzone 3 g/100 mL; Homosalate 15 g/100 mL; Octisalate 5 g/100 mL; Octocrylene 2.8 g/100 mL; Oxybenzone 6 g/100 mL
INACTIVE INGREDIENTS: YELLOW WAX; BUTYLATED HYDROXYTOLUENE; CAPRYLYL TRISILOXANE; DIMETHICONE; Dimethyl Capramide; GLYCYRRHIZINATE DIPOTASSIUM; EDETATE DISODIUM; Ethylhexylglycerin; Ethylhexyl Stearate; GLYCERYL MONOSTEARATE; Hydrated Silica; Methylisothiazolinone; PEG-100 Stearate; POLIHEXANIDE; POLYESTER-8 (1400 MW, CYANODIPHENYLPROPENOYL CAPPED); Trideceth-6; Water; Xanthan Gum

Drug Facts

Active ingredients Purpose
Avobenzone 3.0%..................................................................Sunscreen
Homosalate 15.0%.................................................................Sunscreen
Octisalate 5.0%......................................................................Sunscreen
Octocrylene 2.8%...................................................................Sunscreen
Oxybenzone 6.0%..................................................................Sunscreen

INDICATIONS AND USAGE

Uses • helps prevent sunburn

Warnings
For external use only
Do not use on damaged or broken skin
When using this product keep out of eyes. Rinse with water to remove.
Stop use and ask a doctor if rash occurs

Keep out of reach of children. If product is swallowed, get medical help or
contact a Poison Control Center right away

DOSAGE AND ADMINISTRATION

Directions • Apply liberally 15 minutes before sun exposure
• Reapply: • after 80 minutes of swimming or sweating • immediately after
towel drying • at least every 2 hours • Sun Protection Measures. Spending
time in the sun increases your risk of skin cancer and early skin aging. To
decrease this risk, regularly use a sunscreen with a broad spectrum SPF of 15
or higher and other sun protection measures including: • limit time in the sun,
especially from 10 a.m. – 2 p.m. • wear long-sleeve shirts, pants, hats, and
sunglasses • Children under 6 months: Ask a doctor

Other information • protect this product from excessive heat and
direct sun • may stain fabrics

Inactive ingredients

Acrylates/C12-22 Alkyl Methacrylate
Copolymer, Beeswax, BHT, Caprylyl Methicone, Cetyl Dimethicone,
Dimethicone, Dimethyl Capramide, Dipotassium Glycyrrhizate, Disodium EDTA,
Ethylhexyl Stearate, Ethylhexylglycerin, Fragrance,
Glyceryl Stearate, Methylisothiazolinone, PEG-100
Stearate, Polyaminopropyl Biguanide, Polyester-8, Silica,
Sodium Polyacrylate, Styrene/Acrylates Copolymer,
Trideceth-6, Trimethylsiloxysilicate, Water, Xanthan Gum